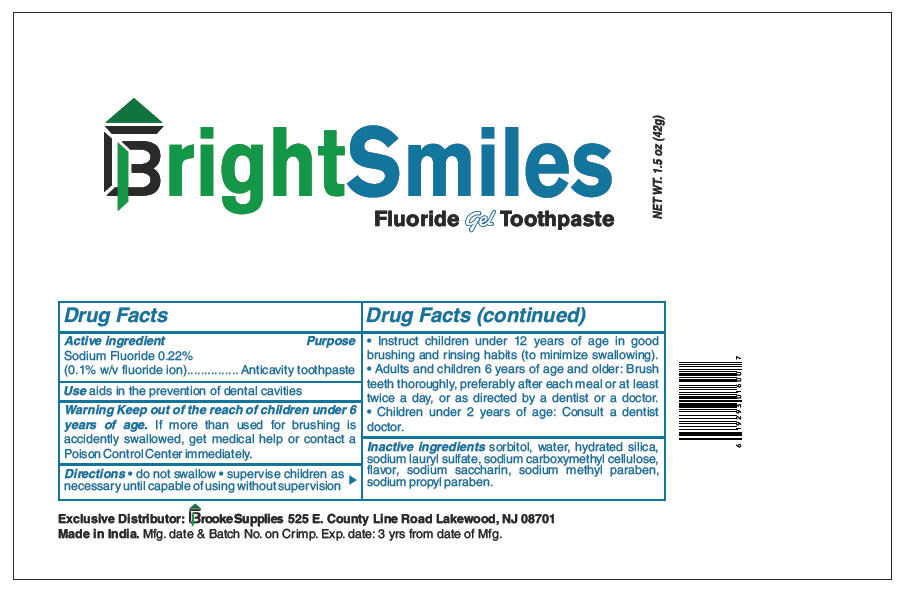 DRUG LABEL: Bright Smiles
NDC: 71074-109 | Form: GEL, DENTIFRICE
Manufacturer: Brooke Supplies
Category: otc | Type: HUMAN OTC DRUG LABEL
Date: 20170127

ACTIVE INGREDIENTS: Sodium Fluoride 0.1 g/100 g
INACTIVE INGREDIENTS: SORBITOL; WATER; HYDRATED SILICA; SODIUM LAURYL SULFATE; CARBOXYMETHYLCELLULOSE SODIUM, UNSPECIFIED FORM; SACCHARIN SODIUM; METHYLPARABEN SODIUM; PROPYLPARABEN SODIUM

Bright Smiles

Drug Facts

Active ingredient

Sodium Fluoride 0.22%
(0.1% w/v fluoride ion)

Purpose

Anticavity toothpaste

Use

aids in the prevention of dental cavities

Warning

KEEP OUT OF REACH OF CHILDREN

Keep out of the reach of children under 6 years of age. If more than used for brushing is accidently swallowed, get medical help or contact a Poison Control Center immediately.

Directions

- do not swallow
- supervise children as necessary until capable of using without supervision
- Instruct children under 12 years of age in good brushing and rinsing habits (to minimize swallowing).
- Adults and children 6 years of age and older: Brush teeth thoroughly, preferably after each meal or at least twice a day, or as directed by a dentist or a doctor.
- Children under 2 years of age: Consult a dentist doctor.

Inactive ingredients

sorbitol, water, hydrated silica, sodium lauryl sulfate, sodium carboxymethyl cellulose, flavor, sodium saccharin, sodium methyl paraben, sodium propyl paraben.

PRINCIPAL DISPLAY PANEL - 42 g Tube Label

BrightSmiles

Fluoride Gel Toothpaste

NET WT. 1.5 oz (42g)